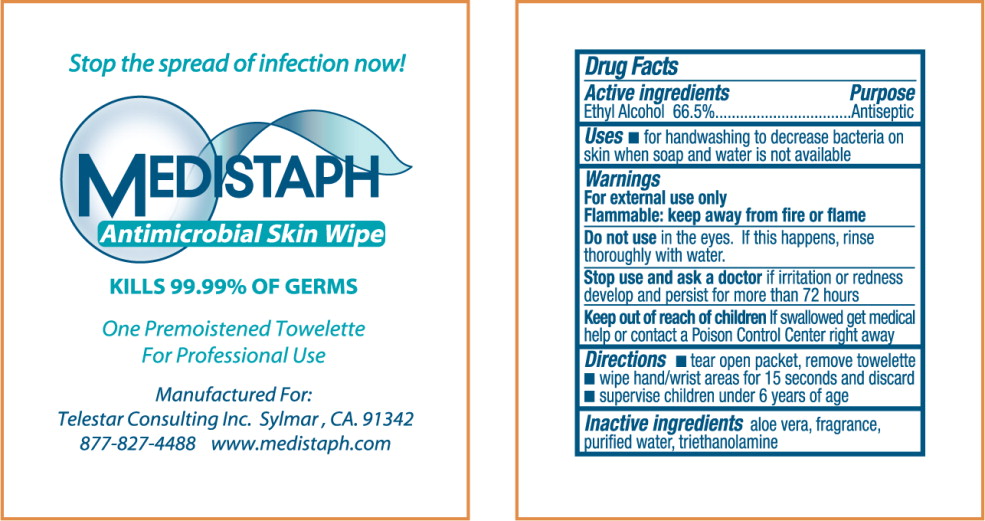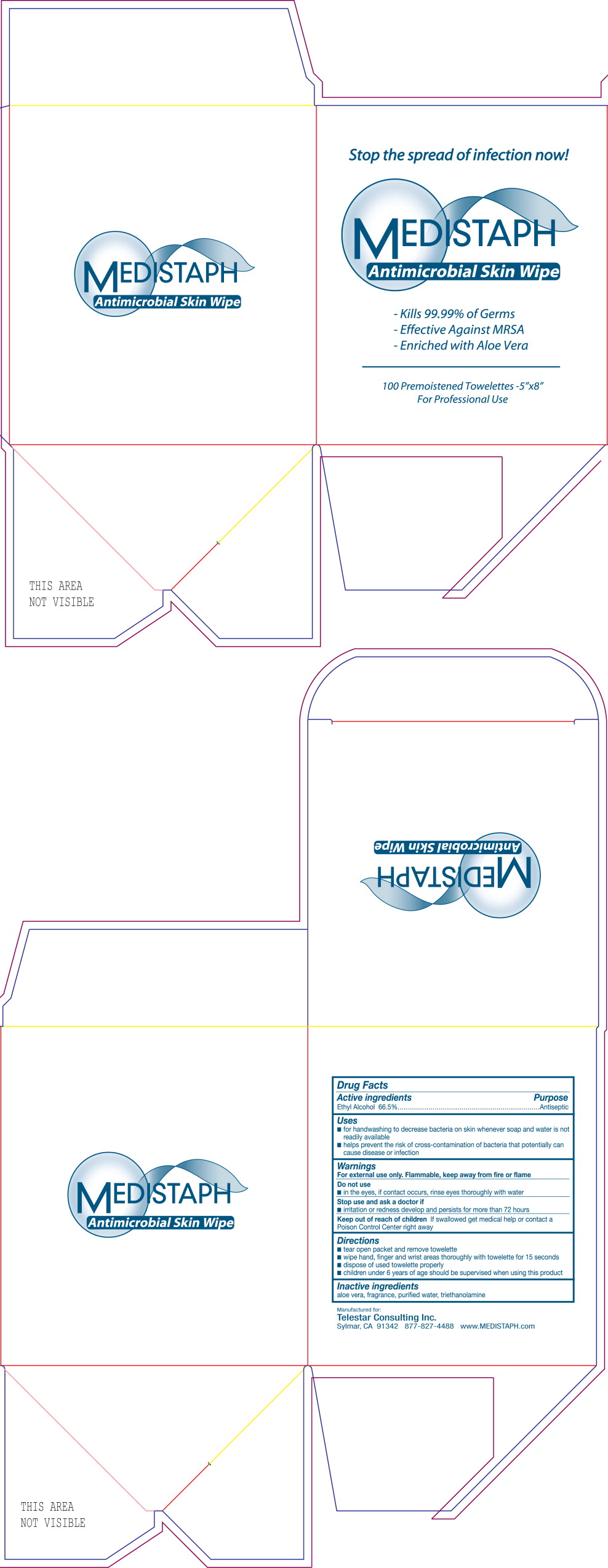 DRUG LABEL: Antiseptic
NDC: 51718-3111 | Form: LIQUID
Manufacturer: Telestar Consulting
Category: otc | Type: HUMAN OTC DRUG LABEL
Date: 20120320

ACTIVE INGREDIENTS: alcohol 665 mL/1 L
INACTIVE INGREDIENTS: aloe vera leaf; water; trolamine

MEDISTAPH
ANTIMICROBIAL SKIN WIPE

Drug Facts

Active Ingredients

Ethyl Alcohol 66.5%

Purpose

Antiseptic

Uses

- for handwashing to decrease bacteria on skin whenever soap and water is not readily available
- helps prevent the risk of cross-contamination of bacteria that potentially can cause disease or infection

Warnings

For external use only

Flammable: keep away from fire or flame

Do not use

- in the eyes, if contact occurs, rinse eyes thoroughly with water.

Stop use and ask doctor if

- irritation or redness develop and persist for more than 72 hours

Keep out of reach of children If swallowed get medical help or contact a Poison Control Center right away

Directions

- tear open packet, remove towelette
- wipe hand, finger and wrist areas thoroughly with towelette for 15 seconds
- dispose of used towelette properly
- children under 6 years of age should be supervised when using this product

Inactive ingredients

aloe vera, fragrance, purified water, triethanolamine

PRINCIPAL DISPLAY PANEL – Antimicrobial Skin Wipe packet

Stop the spread of infection now!

MEDISTAPH

Antimicrobial Skin Wipe

KILLS 99.99% OF GERMS

One Premoistened Towelette
For Professional Use

Manufactured For:
Telestar Consulting Inc. Sylmar, CA. 91342
877-827-4488 www.medistaph.com

PRINCIPAL DISPLAY PANEL – Antimicrobial Skin Wipe box

Stop the spread of infection now!

MEDISTAPH

Antimicrobial Skin Wipe

Kills 99.99% of Germs
Effective Against MRSA
Enriched with Aloe Vera

100 Premoistened Towelette – 5”x8”
For Professional Use